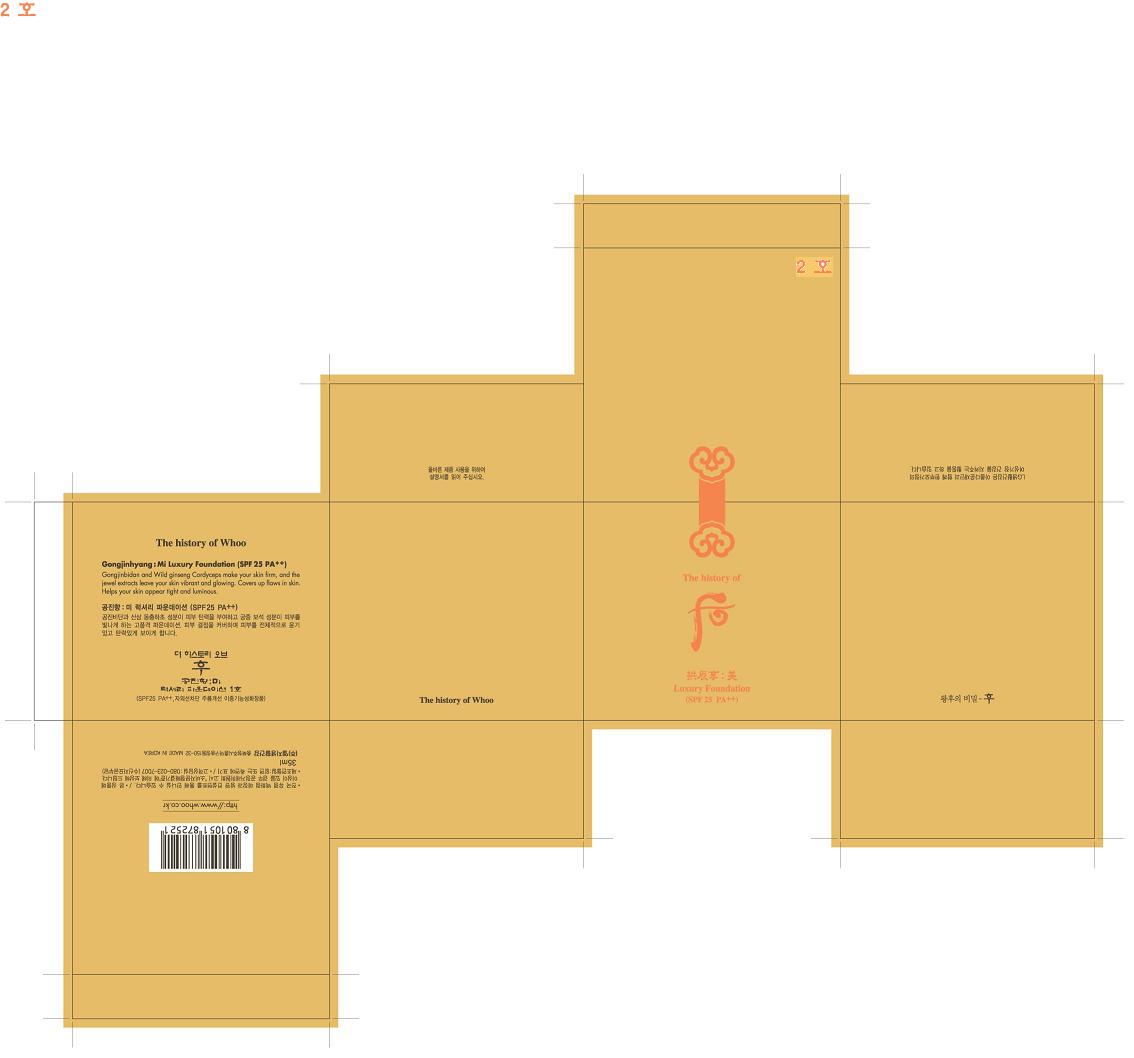 DRUG LABEL: GONGJINHYANG MI LUXURY FOUNDATION 2
NDC: 53208-410 | Form: CREAM
Manufacturer: LG Household and Healthcare, Inc.
Category: otc | Type: HUMAN OTC DRUG LABEL
Date: 20100330

ACTIVE INGREDIENTS: HYDROXYPROLINE 0.53 mL/100 mL; OCTINOXATE 1 mL/100 mL
INACTIVE INGREDIENTS: WATER; ETHYLHEXYL PALMITATE; SUCCINIC ACID; CAPRYLIC/CAPRIC MONO/DIGLYCERIDES; CYCLOMETHICONE 5; BUTYLENE GLYCOL; ADIPIC ACID; GLYCERIN; PARAFFIN; MAGNESIUM SULFATE; HYDROXYPROLINE; DIMETHICONE; PHENOXYETHANOL; SORBITAN OLIVATE; STEARIC ACID; METHYLPARABEN; ETHYLPARABEN; ALPHA-TOCOPHEROL ACETATE; PROPYLPARABEN; GOLD

GONGJINHYANG MI LUXURY FOUNDATION 2

ACTIVE INGREDIENT

OCTINOXATE 1.00g/100g

HYDROXYPROLINE 0.53g/100g

WARNINGS AND PRECAUTIONS

For external use only

Keep out of reach of children. Is swallowed, get medical help or contact a Poison Control Center right away.

WHEN USING

Keep out of eyes. Rinse with water to remove.

Stop use if a rash or irritation develops and lasts.

PACKAGE LABEL

The History of Whoo

Luxury Foundation 2